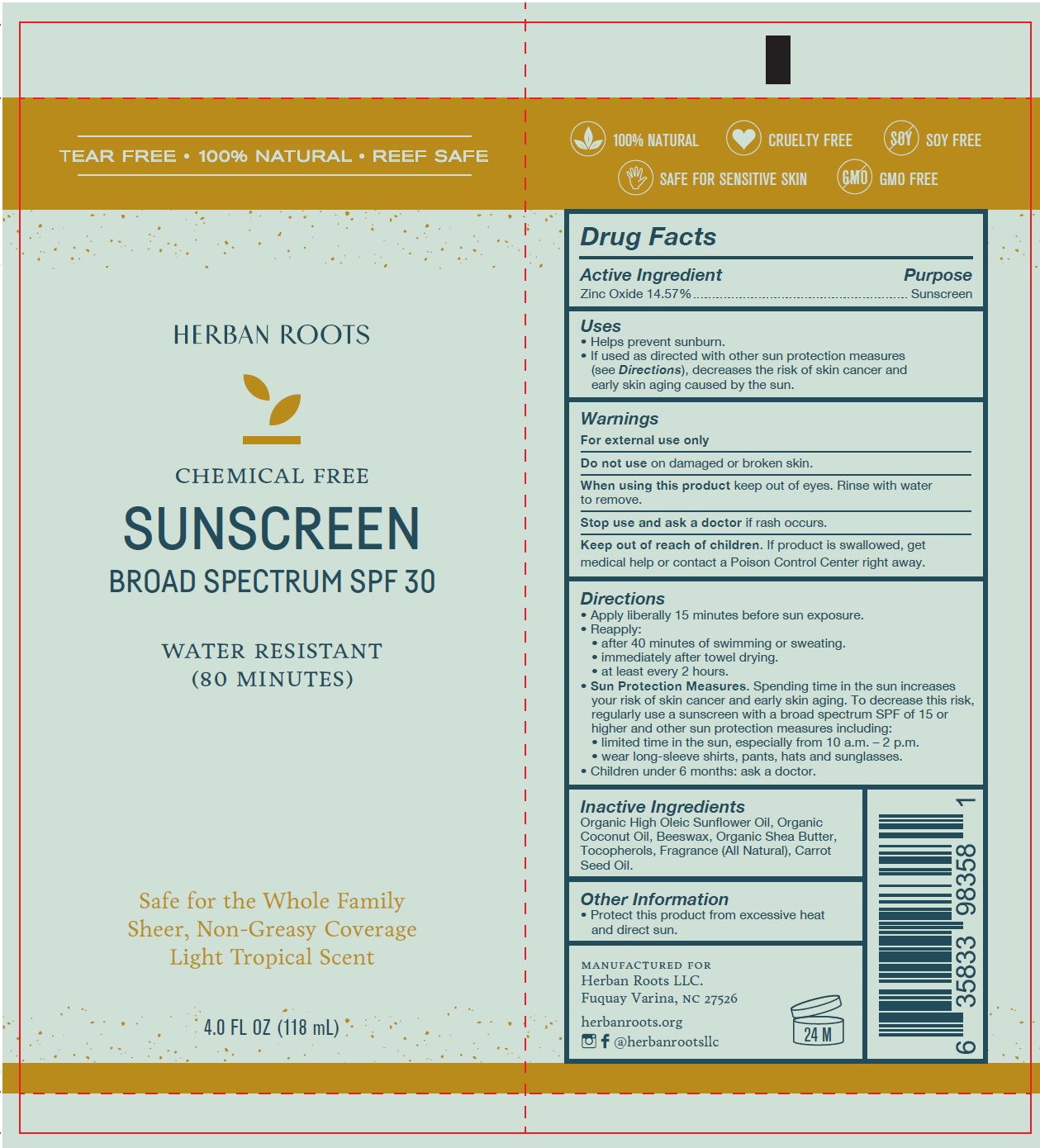 DRUG LABEL: Chemical Free Sunscreen
NDC: 72209-001 | Form: LOTION
Manufacturer: Herban Roots, LLC
Category: otc | Type: HUMAN OTC DRUG LABEL
Date: 20241231

ACTIVE INGREDIENTS: ZINC OXIDE 145.7 mg/1 mL
INACTIVE INGREDIENTS: CARROT SEED OIL; SUNFLOWER OIL; COCONUT OIL; YELLOW WAX; SHEA BUTTER; TOCOPHEROL

Chemical Free Sunscreen

Active Ingredient

Zinc Oxide 14.57%

Purpose

Sunscreen

Uses

- Helps prevent sunburn.
- If used as directed with other sun protection measures (see Directions), decreases the risk of skin cancer and early skin aging caused by the sun.

Warnings

For external use only

Do not use

on damaged or broken skin.

When using this product

keep out of eyes. Rinse with water to remove.

Stop use and ask a doctor

if rash occurs.

Keep out of reach of children.

If product is swallowed, get medical help or contact a Poison Control Center right away.

Directions

- Apply liberally 15 minutes before sun exposure.
- Reapply:
- after 40 minutes of swimming or sweating.
- immediately after towel drying.
- at least every 2 hours.
- Sun Protection Measures. Spending time in the sun increases your risk of skin cancer and early skin aging. To decrease this risk, regularly use a sunscreen with a broad spectrum SPF of 15 or higher and other sun protection measures including:
- limited time in the sun, especially from 10 a.m. – 2 p.m.
- wear long-sleeve shirts, pants, hats and sunglasses.
- Children under 6 months: ask a doctor.

Inactive Ingredients:

Organic High Oleic Sunflower Oil, Organic Coconut Oil, Beeswax, Organic Shea Butter, Tocopherols, Fragrance (All Natural), Carrot Seed Oil.

Other Information

- Protect this product from excessive heat and direct sun.